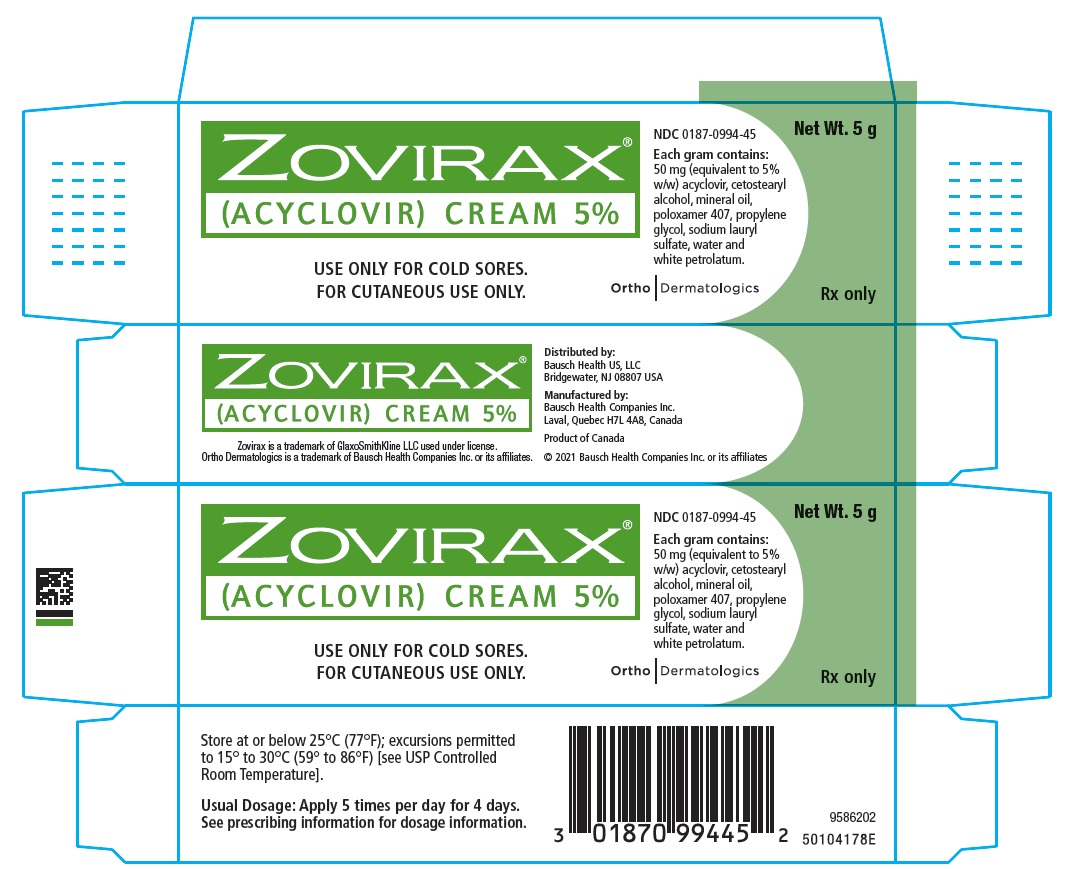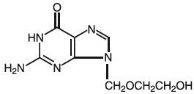 DRUG LABEL: Zovirax
NDC: 0187-0994 | Form: CREAM
Manufacturer: Bausch Health US, LLC
Category: prescription | Type: HUMAN PRESCRIPTION DRUG LABEL
Date: 20210201

ACTIVE INGREDIENTS: acyclovir 50 mg/1 g
INACTIVE INGREDIENTS: Cetostearyl alcohol; Mineral oil; Poloxamer 407; Sodium lauryl sulfate; Water; Petrolatum; Propylene glycol

HIGHLIGHTS OF PRESCRIBING INFORMATION

These highlights do not include all the information needed to use ZOVIRAX Cream safely and effectively. See full prescribing information for ZOVIRAX Cream.
ZOVIRAX® (acyclovir) cream, for topical use
Initial U.S. Approval: 2002

1 INDICATIONS AND USAGE

ZOVIRAX Cream is a herpes simplex virus (HSV) deoxynucleoside analogue DNA polymerase inhibitor indicated for the treatment of recurrent herpes labialis (cold sores) in immunocompetent adults and adolescents 12 years of age and older. (1)

2 DOSAGE AND ADMINISTRATION

- Apply 5 times a day for 4 days. (2)
- Administer immediately following the onset of cold sore lesions. (2)

3 DOSAGE FORMS AND STRENGTHS

- Cream, 50 mg (equivalent to 5% w/w) acyclovir. (3)

4 CONTRAINDICATIONS

- ZOVIRAX Cream is contraindicated in patients with known hypersensitivity to acyclovir, valacyclovir or any component of the formulation. (4)

5 WARNINGS AND PRECAUTIONS

- Only for topical use of recurrent HSV lesions on the external aspect of lips and the face. ZOVIRAX Cream should not be applied on mucous membranes including in the eye or inside the mouth or nose. (5.1)
- There is a potential for irritation and contact sensitization. (5.2)

6 ADVERSE REACTIONS

- The most common adverse reactions reported were local skin reactions at the application site. (6.1)
- Angioedema, anaphylaxis, contact dermatitis and eczema have been reported. (6.2)

To report SUSPECTED ADVERSE REACTIONS, contact Bausch Health US, LLC at 1-800-321-4576 or FDA at 1-800-FDA-1088 or www.fda.gov/medwatch.

7 DRUG INTERACTIONS

- Clinical experience has identified no interactions resulting from topical or systemic administration of other drugs concomitantly with ZOVIRAX Cream. Due to minimal systemic absorption of ZOVIRAX Cream, systemic drug interactions are unlikely. (7)

FULL PRESCRIBING INFORMATION

1 INDICATIONS AND USAGE

ZOVIRAX Cream is a herpes simplex virus (HSV) deoxynucleoside analogue DNA polymerase inhibitor indicated for the treatment of recurrent herpes labialis (cold sores) in immunocompetent adults and adolescents 12 years of age and older.

2 DOSAGE AND ADMINISTRATION

ZOVIRAX Cream should be applied 5 times per day for 4 days. Therapy should be initiated as early as possible following the onset of signs or symptoms of herpes labialis, i.e. during the prodrome or when lesions appear.

For adolescents 12 years of age and older, the dosage is the same as in adults.

3 DOSAGE FORMS AND STRENGTHS

Each gram of ZOVIRAX Cream contains 50 mg (equivalent to 5% w/w) of acyclovir.

4 CONTRAINDICATIONS

ZOVIRAX Cream is contraindicated in patients with known hypersensitivity to acyclovir, valacyclovir, or any component of the formulation.

5 WARNINGS AND PRECAUTIONS

5.1 General

ZOVIRAX Cream should only be applied on the affected external aspects of the lips and face in patients with herpes labialis. Because no data are available, application to human mucous membranes is not recommended. ZOVIRAX Cream is intended for cutaneous use only and should not be used in the eye or inside the mouth or nose.

5.2 Contact Sensitization

ZOVIRAX Cream has a potential for irritation and contact sensitization [see Adverse Reactions (6.1)].

The effect of ZOVIRAX Cream has not been established in immunocompromised patients.

6 ADVERSE REACTIONS

6.1 Clinical Trials Experience

Because clinical trials are conducted under widely varying conditions, adverse reaction rates observed in the clinical trials of a drug cannot be directly compared to rates in the clinical trials of another drug, and may not reflect the rates observed in clinical practice.

In five double-blind, placebo-controlled trials, 1124 patients were treated with ZOVIRAX Cream and 1161 with placebo (vehicle) cream. Local application site reactions were reported by 5% of patients receiving ZOVIRAX Cream and 4% of patients receiving placebo. The most common adverse reactions at the site of topical application were dry lips, desquamation, dryness of skin, cracked lips, burning skin, pruritus, flakiness of skin, and stinging on skin; each adverse reaction occurred in less than 1% of patients receiving ZOVIRAX Cream and placebo. Three patients on ZOVIRAX Cream and one patient on placebo discontinued treatment due to an adverse event.

An additional study, enrolling 22 healthy adults, was conducted to evaluate the dermal tolerance of ZOVIRAX Cream compared with vehicle using single occluded and semi-occluded patch testing methodology. Both ZOVIRAX Cream and placebo showed a high and cumulative irritation potential. Another study, enrolling 251 healthy adults, was conducted to evaluate the contact sensitization potential of ZOVIRAX Cream using repeat insult patch testing methodology. Of 202 evaluable subjects, possible cutaneous sensitization reactions were observed in the same 4 (2%) subjects with both ZOVIRAX Cream and placebo, and these reactions to both ZOVIRAX Cream and placebo were confirmed in 3 subjects upon rechallenge. The sensitizing ingredient(s) has not been identified.

The safety profile in patients 12 to 17 years of age was similar to that observed in adults.

6.2 Postmarketing Experience

In addition to adverse events reported from clinical trials, the following events have been identified during postapproval use of acyclovir cream. Because they are reported voluntarily from a population of unknown size, estimates of frequency cannot be made. These events have been chosen for inclusion due to a combination of their seriousness, frequency of reporting, or potential causal connection to acyclovir cream.

General: Angioedema, anaphylaxis.

Skin: Contact dermatitis, eczema.

7 DRUG INTERACTIONS

Clinical experience has identified no interactions resulting from topical or systemic administration of other drugs concomitantly with ZOVIRAX Cream. Due to minimal systemic absorption of ZOVIRAX Cream, systemic drug interactions are unlikely.

8 USE IN SPECIFIC POPULATIONS

8.1 Pregnancy

Risk Summary

Acyclovir is minimally absorbed systemically following topical route of administration, and maternal use is not expected to result in fetal exposure to the ZOVIRAX Cream [see Clinical Pharmacology (12.3)]. Experience with topical acyclovir use in pregnant women over several decades, based on published literature including observational studies, has not identified a drug-associated risk of major birth defects, miscarriage or adverse maternal or fetal outcomes. Animal reproduction studies with systemic exposure of acyclovir have been conducted. Refer to acyclovir prescribing information for additional details.

The estimated background risk of major birth defects and miscarriage for the indicated population is unknown. All pregnancies have a background risk of birth defect, loss, or other adverse outcomes. In the U.S. general population, the estimated background risk of major birth defects and miscarriage in clinically recognized pregnancies is 2% to 4% and 15% to 20%, respectively.

8.2 Lactation

Risk Summary

Acyclovir is minimally absorbed systemically following topical route of administration, and breastfeeding is not expected to result in exposure of the child to ZOVIRAX Cream [see Clinical Pharmacology (12.3)]. There are no data on the effects of ZOVIRAX on the breastfed infant or on milk production. The developmental and health benefits of breastfeeding should be considered along with the mother’s clinical need for ZOVIRAX Cream and any potential adverse effects on the breastfed child from ZOVIRAX Cream or from the underlying maternal condition.

8.4 Pediatric Use

An open-label, uncontrolled trial with ZOVIRAX Cream was conducted in 113 patients aged 12 to 17 years with recurrent herpes labialis. In this trial, therapy was applied using the same dosing regimen as in adults and subjects were followed for adverse events. The safety profile was similar to that observed in adults. Safety and effectiveness in pediatric patients less than 12 years of age have not been established.

8.5 Geriatric Use

Clinical studies of acyclovir cream did not include sufficient numbers of subjects aged 65 and over to determine whether they respond differently from younger subjects. Other reported clinical experience has not identified differences in responses between the elderly and younger patients. Systemic absorption of acyclovir after topical administration is minimal [see Clinical Pharmacology (12.3)].

10 OVERDOSAGE

Overdosage by topical application of ZOVIRAX Cream is unlikely because of minimal systemic exposure [see Clinical Pharmacology (12.3)]. There is no information available for overdose.

11 DESCRIPTION

ZOVIRAX is the brand name for acyclovir, a synthetic deoxynucleoside analogue active against herpes viruses. ZOVIRAX Cream 5% is a formulation for topical administration.

The chemical name of acyclovir is 2-amino-1,9-dihydro-9-[(2-hydroxyethoxy) methyl]-6H-purin-6-one; it has the following structural formula:

Acyclovir is a white, crystalline powder with the molecular formula C8H11N5O3 and a molecular weight of 225. The maximum solubility in water at 37°C is 2.5 mg/mL. The pKa’s of acyclovir are 2.27 and 9.25.

Each gram of ZOVIRAX Cream contains 50 mg (equivalent to 5% w/w) of acyclovir and the following inactive ingredients: cetostearyl alcohol, mineral oil, poloxamer 407, propylene glycol, sodium lauryl sulfate, water and white petrolatum.

12 CLINICAL PHARMACOLOGY

12.1 Mechanism of Action

Acyclovir is an antiviral drug active against α-herpesviruses [see Microbiology (12.4)].

12.3 Pharmacokinetics

A clinical pharmacology study was performed with ZOVIRAX Cream in adult volunteers to evaluate the percutaneous absorption of acyclovir. In this study, which included 6 male volunteers, the cream was applied to an area of 710 cm^2 on the backs of the volunteers 5 times daily at intervals of 2 hours for a total of 4 days. The weight of cream applied and urinary excretion of acyclovir were measured daily. Plasma concentration of acyclovir was assayed 1 hour after the final application. The average daily urinary excretion of acyclovir was approximately 0.04% of the daily applied dose. Plasma acyclovir concentrations were below the limit of detection (0.01 μM) in 5 subjects and barely detectable (0.014 μM) in 1 subject. Systemic absorption of acyclovir from ZOVIRAX Cream is minimal in adults.

The systemic absorption of acyclovir following topical application of cream has not been evaluated in patients <18 years of age.

12.4 Microbiology

Mechanism of Action: Acyclovir is a synthetic purine deoxynucleoside analogue with cell culture and in vivo inhibitory activity against HSV types 1 (HSV-1) and 2 (HSV-2) DNA polymerases. It inhibits HSV-1 and HSV-2 replication in cell culture and in vivo.

The inhibitory activity of acyclovir is selective due to its affinity for the enzyme thymidine kinase (TK) encoded by HSV. This viral enzyme converts acyclovir into acyclovir monophosphate, a deoxynucleotide analogue. The monophosphate is further converted into diphosphate by cellular guanylate kinase and into triphosphate by a number of cellular enzymes. In biochemical assays, acyclovir triphosphate inhibits replication of α-herpes viral DNA. This inhibition is accomplished in 3 ways: 1) competitive inhibition of viral DNA polymerase, 2) incorporation into and termination of the growing viral DNA chain, and 3) inactivation of the viral DNA polymerase.

Antiviral Activity

The quantitative relationship between the susceptibility of herpes viruses to antivirals in cell culture and the clinical response to therapy has not been established in humans, and virus sensitivity testing has not been standardized. Sensitivity testing results, expressed as the concentration of drug required to inhibit by 50% the growth of virus in cell culture (EC50 value), vary greatly depending upon a number of factors. Using plaque-reduction assays on Vero cells, the EC50 values of acyclovir against herpes simplex virus isolates range from 0.09 to 59.9 μM (0.02 to 13.5 μg/mL) for HSV-1 and from 0.04 to 44.0 μM (0.01 to 9.9 μg/mL) for HSV-2.

Resistance

In Cell Culture

Acyclovir-resistant HSV-1 and HSV-2 strains were isolated in cell culture. Acyclovir-resistant HSV resulted from mutations in the viral thymidine kinase (TK; pUL23) and DNA polymerase (POL; pUL30) genes. Frameshifts were commonly isolated and result in premature truncation of the HSV TK product with consequent decreased susceptibility to acyclovir. Mutations in the viral TK gene may lead to complete loss of TK activity (TK negative), reduced levels of TK activity (TK partial), or alteration in the ability of viral TK to phosphorylate the drug without an equivalent loss in the ability to phosphorylate thymidine (TK altered). In cell culture the following resistance-associated substitutions in TK of HSV-1 and HSV-2 were observed (Table 1).

Table 1: Summary of Acyclovir (ACV) Resistance-associated Amino Acid Substitutions in Cell Culture
HSV-1 | TK | P5A, H7Q, L50V, G56V, G59A, G61A, K62N, T63A, E83K, P84S, D116N, P131S, R163H, A167V, P173L, Q185R, R216S, R220H, T245M, R281stop, T287M, M322K
HSV-2 | TK | L69P, C172R, T288M
HSV-1 | POL | D368A, Y557S, E597D, V621S, L702H, N815S, V817M, G841C
HSV-2 | POL | -

In HSV-Infected Patients

Clinical HSV-1 and HSV-2 isolates obtained from patients who failed treatment for their α-herpesvirus infections were evaluated for genotypic changes in the TK and POL genes and for phenotypic resistance to acyclovir (Table 2). HSV isolates with frameshift mutations and resistance-associated substitutions in TK and POL were identified. The listing of substitutions in HSV TK and POL leading to decreased susceptibility to acyclovir is not all inclusive and additional changes will likely be identified in HSV variants isolated from patients who fail acyclovir-containing regimens. The possibility of viral resistance to acyclovir should be considered in patients who fail to respond or experience recurrent viral shedding during therapy.

Table 2: Summary of ACV Resistance-associated Amino Acid Substitutions Observed in Treated Patients
HSV-1 | TK | G6C, R32H, R41H, R51W, Y53C/D/H, Y53stop, D55N, G56D/S, P57H, H58/N/R/Y, G59R, G61A, K62N, T63I, Q67stop, S74stop, Y80N, E83K, P84L, Y87H, W88R, R89Q/W, E95stop, T103P, Q104H, Q104stop, H105P, D116N, M121L/R, S123R, Q125H, M128L, G129D, I143V, A156V, D162A/H/N, R163G/H, L170P, Y172C, P173L, A174P, A175V, R176Q/W, R176stop, L178R, S181N, V187M, A189V, V192A, G200C/D/S, T201P, V204G, A207P, L208F/H, R216C/H, R220C/H, R221H, R222C/H, L227F, T245M/P, L249P, Q250Stop, C251G, R256W, E257K, Q261R, T287M, L288Stop, L291P/R, L297S, L315S, L327R, C336Y, Q342Stop, T354P, L364P, A365T
HSV-2 | TK | R34C, G39E, R51W, Y53N, G59P, G61W, S66P, A72S, D78N, P85S, A94V, N100H, I101S, Q105P, T131P, D137stop, F140L, L158P, S169P, R177W, S182N, M183I, V192M, G201D, R217H, R221C/H, Q222stop, R223H, Y239stop, R271V, P272S, D273R, T287M, C337Y
HSV-1 | POL | K532T, Q570R, L583V, A605V, A657T, D672N, V715G, A719T/V, S724N, F733C, E771Q, S775N, L778M, E798K, V813M, N815S, G841S, I890M, G901V, V958L H1228D
HSV-2 | POL | E250Q, D307N, K533E, A606V, C625R, R628C, E678G, A724V, S725G, S729N, I731F, Q732R, M789K/T, V818A, N820S, Y823C, Q829R, T843A, M910T, D912N/V, A915V, F923L, T934A, R964H

Note: Additional substitutions to acyclovir resistance may exist.

Cross-resistance

Cross-resistance has been observed among HSV isolates carrying frameshift mutations and resistance-associated substitutions, which confer reduced susceptibility to penciclovir (PCV), famciclovir (FCV), and foscarnet (FOS) [Table 3].

Table 3: Summary of Amino Acid Substitutions Conferring Cross-Resistance to PCV, FCV or FOS
Cross-resistant to PCV/FCV | HSV-1 TK | G6C, R32H, R51W, Y53C/H, H58N, G61A, S74Stop, E83K, P84L, T103P, Q104Stop, D116N, M121R, I143V, R163H, L170P, Y172C, A174P, R176Q/W, Q185R, A189V, G200D, L208H, R216C, R220H, R222C/H, T245M, Q250Stop, R256W, R281Stop, T287M, L315S, M322K, C336Y
Cross-resistant to PCV/FCV | HSV-1 POL | A657T, D672N, V715G, A719V, S724N, E798K, N815S, G841S
Cross-resistant to PCV/FCV | HSV-2 TK | G39E, R51W, Y53N, R177W, R221H, T288M
Cross-resistant to PCV/FCV | HSV-2 POL | K533E, A606V, C625R, R628C, S729N, Q732R, M789K/T, V818A, N820S, F923L, T934A
Cross-resistant to FOS | HSV-1 POL | D368A, A605V, D672N, L702H, V715G, A719T/V, S724N, L778M, E798K, V813M, N815S, V817M, G841C/S, I890M
Cross-resistant to FOS | HSV-2 POL | K533E, A606V, C625R, R628C, A724V, S725G, S729N, I731F, Q732R, M789K/T, V818A, Y823C, D912V, F923L, T934A, R964H

13 NONCLINICAL TOXICOLOGY

13.1 Carcinogenesis, Mutagenesis, Impairment of Fertility

Systemic exposure following topical administration of acyclovir is minimal. Dermal carcinogenicity studies were not conducted. Results from the studies of carcinogenesis, mutagenesis and fertility are not included in the full prescribing information for ZOVIRAX Cream due to the minimal exposures of acyclovir that result from dermal application. Information on these studies is available in the full prescribing information for ZOVIRAX Capsules, Tablets, and Suspension and ZOVIRAX for Injection.

14 CLINICAL STUDIES

14.1 Adult Subjects

ZOVIRAX Cream was evaluated in two double-blind, randomized, placebo (vehicle)-controlled trials for the treatment of recurrent herpes labialis. The average patient had five episodes of herpes labialis in the previous 12 months. In the first trial, the median age of subjects was 37 years (range 18 to 81 years), 74% were female, and 94% were Caucasian. In the second trial, median age of subjects was 38 years (range 18 to 87 years), 73% were female, and 94% were Caucasian. Subjects were instructed to initiate treatment within 1 hour of noticing signs or symptoms and continue treatment for 4 days, with application of study medication 5 times per day. In both studies, the mean duration of the recurrent herpes labialis episode was approximately one-half day shorter in the subjects treated with ZOVIRAX Cream (n = 682) compared with subjects treated with placebo (n = 703) for approximately 4.5 days versus 5 days, respectively. No significant difference was observed between subjects receiving ZOVIRAX Cream or placebo in the prevention of progression of cold sore lesions.

14.2 Pediatric Subjects

An open-label, uncontrolled trial with ZOVIRAX Cream was conducted in 113 patients aged 12 to 17 years with recurrent herpes labialis. In this trial, therapy was applied using the same dosing regimen as in adults and subjects were followed for adverse events. The safety profile was similar to that observed in adults.

16 HOW SUPPLIED/STORAGE AND HANDLING

Each gram of ZOVIRAX Cream contains 50 mg (equivalent to 5% w/w) of acyclovir in an aqueous cream base. ZOVIRAX Cream is supplied as follows:

NDC 0187-0994-45: 5 g tubes

Store at or below 25°C (77°F); excursions permitted to 15° to 30°C (59° to 86°F) [see USP Controlled Room Temperature].

17 PATIENT COUNSELING INFORMATION

Advise the patient to read the FDA-approved patient labeling (Patient Information).

General

Patients should be informed that ZOVIRAX Cream is a prescription topical cream for the treatment of cold sores (recurrent herpes labialis) that occur on the face and lips. ZOVIRAX Cream is not a cure for cold sores. Patients should be instructed that ZOVIRAX Cream is intended for cutaneous use only for herpes labialis of the lips and around the mouth. Patients should be advised that ZOVIRAX Cream should not be used in the eye, inside the mouth or nose, or on the genitals. Patients should be instructed to avoid applying other topical products to the affected area while using ZOVIRAX Cream.

Do not use if you are allergic to ZOVIRAX Cream or any of the ingredients in ZOVIRAX Cream. Before you use ZOVIRAX Cream, tell your doctor if you are pregnant, planning to become pregnant, or are breast-feeding.

Instructions for Use

Treatment should be initiated at the earliest sign or symptom of recurrence. Instruct patients to wash hands prior to application and ensure the face and/or lips are clean and dry. Advise patients to apply ZOVIRAX Cream topically 5 times per day for 4 days. Instruct patients to topically apply a quantity of ZOVIRAX Cream sufficient to cover the affected area, including the outer margin. Advise patients to avoid unnecessary rubbing of the affected area to avoid aggravating or transferring the infection. Instruct patients to wash their hands with soap and water after using ZOVIRAX Cream. Keep out of reach of children.

Possible Side Effects

Common skin-related side effects that occurred when ZOVIRAX Cream was applied include application site reactions. ZOVIRAX Cream has the potential for irritation and contact sensitization.

Distributed by: Bausch Health US, LLC
Bridgewater, NJ 08807 USA

Manufactured by: Bausch Health Companies Inc.
Laval, Quebec H7L 4A8, Canada

Zovirax is a trademark of GlaxoSmithKline LLC used under license.

© 2021 Bausch Health Companies Inc. or its affiliates

9462203

PATIENT INFORMATION

ZOVIRAX (zho-vahy-rex)
(acyclovir)
Cream

Important information: ZOVIRAX Cream is for use on cold sores on the lips and around the mouth only. ZOVIRAX Cream should not be used in your eyes, mouth, nose, or on your genitals.

What is ZOVIRAX Cream?

- ZOVIRAX Cream is a prescription medicine used to treat cold sores (herpes labialis) that are recurring in adults and children 12 years of age and older, and who have normal immune systems.
- ZOVIRAX Cream is not a cure for cold sores.

It is not known if ZOVIRAX Cream is safe and effective in children less than 12 years of age.

Do not use ZOVIRAX Cream if you are allergic to acyclovir, valacyclovir, or any of the ingredients in ZOVIRAX Cream. See the end of this leaflet for a complete list of ingredients in ZOVIRAX Cream.

What should I tell my healthcare provider before using ZOVIRAX Cream?

Before using ZOVIRAX Cream, tell your healthcare provider about all of your medical conditions, including if you:

- become sick very easily (have a weak immune system).
- are pregnant or plan to become pregnant. It is not known if ZOVIRAX Cream will harm your unborn baby.
- are breastfeeding or plan to breastfeed. It is not known if ZOVIRAX Cream passes into your breast milk. Talk to your healthcare provider about the best way to feed your baby if you use ZOVIRAX Cream.

Tell your healthcare provider about all the medicines you take, including prescription and over-the-counter medicines, vitamins, and herbal supplements.

How should I use ZOVIRAX Cream?

- Use ZOVIRAX Cream exactly as your healthcare provider tells you to use it.
- Use ZOVIRAX Cream as soon as you have the first symptoms of a cold sore such as itching, redness, burning or tingling, or when the cold sore appears.
- Wash your hands with soap and water before and after applying ZOVIRAX Cream.
- The affected area should be clean and dry before applying ZOVIRAX Cream.
- Apply ZOVIRAX Cream to the affected area 5 times each day for 4 days, including the outer edge.
- You should not apply other skin products to the affected area during treatment with ZOVIRAX Cream.
- Avoid unnecessary rubbing of the cold sore because this may cause the cold sore to spread to other areas around your mouth or make your cold sore worse.

What are the possible side effects of ZOVIRAX Cream?

The most common side effects of ZOVIRAX Cream are skin reactions at the treatment site and may include: dry or cracked lips, peeling, flaking or dryness of the skin, a burning or stinging feeling, and itching.

These are not all the possible side effects of ZOVIRAX Cream. Call your doctor for medical advice about side effects. You may report side effects to FDA at 1-800-FDA-1088.

How should I store ZOVIRAX Cream?

- Store ZOVIRAX Cream at room temperature between 68° to 77°F (20° to 25°C).

Keep ZOVIRAX Cream and all medicines out of reach of children.

General information about the safe and effective use of ZOVIRAX Cream.

Medicines are sometimes prescribed for purposes other than those listed in a Patient Information leaflet. Do not use ZOVIRAX Cream for a condition for which it was not prescribed. Do not give ZOVIRAX Cream to other people, even if they have the same symptoms you have. It may harm them. You can ask your pharmacist or healthcare provider for information about ZOVIRAX Cream that is written for health professionals.

What are the ingredients in ZOVIRAX Cream?

Active ingredient: acyclovir
Inactive ingredients: cetostearyl alcohol, mineral oil, poloxamer 407, propylene glycol, sodium lauryl sulfate, water, and white petrolatum

Distributed by: Bausch Health US, LLC
Bridgewater, NJ 08807 USA

Manufactured by: Bausch Health Companies Inc.
Laval, Quebec H7L 4A8, Canada

Zovirax is a trademark of GlaxoSmithKline LLC used under license.

© 2021 Bausch Health Companies Inc. or its affiliates

For more information, call 1-800-321-4576.

This Patient Information has been approved by the U.S. Food and Drug Administration.

Revised: 02/2021

9462203

PRINCIPAL DISPLAY PANEL - 5g Tube Carton

ZOVIRAX®
(ACYCLOVIR) CREAM 5%

NDC 0187-0994-45
Net Wt. 5 g

Each gram contains:
50 mg (equivalent to 5%
w/w) acyclovir, cetostearyl
alcohol, mineral oil,
poloxamer 407, propylene
glycol, sodium lauryl
sulfate, water and
white petrolatum.

USE ONLY FOR COLD SORES.
FOR CUTANEOUS USE ONLY.

Ortho Dermatologics

Rx only